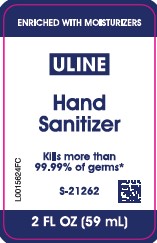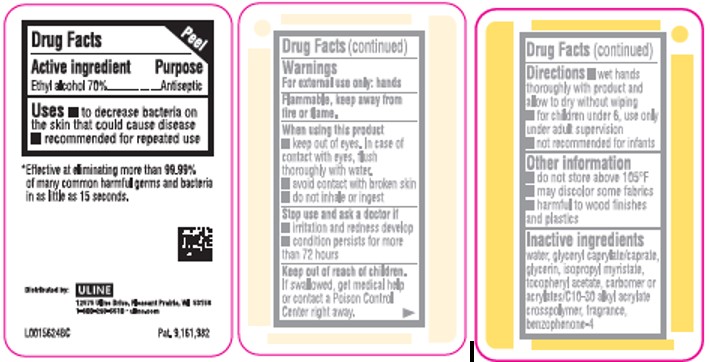 DRUG LABEL: Hand Sanitizer
NDC: 69790-770 | Form: GEL
Manufacturer: Uline
Category: otc | Type: HUMAN OTC DRUG LABEL
Date: 20260217

ACTIVE INGREDIENTS: ALCOHOL 70 mL/100 mL
INACTIVE INGREDIENTS: WATER; GLYCERYL CAPRYLATE/CAPRATE; GLYCERIN; ISOPROPYL MYRISTATE; .ALPHA.-TOCOPHEROL ACETATE; CARBOMER HOMOPOLYMER, UNSPECIFIED TYPE; CARBOMER COPOLYMER TYPE B (ALLYL PENTAERYTHRITOL CROSSLINKED); SULISOBENZONE

Uline 370.001/370AB & AE rev 1
Advanced Hand Sanitizer

Active ingredient

Ethyl alcohol 70%

Purpose

Antiseptic

Uses

- to decrease bacteria on the skin that could cause disease
- recommend for repeated use

Warnings

For external use only: hands

Flammable, keep away from fire and flame.

When using this product

- keep out of eyes. In case of contact with eyes, flush thoroughly with water.
- avoid contact with broken skin
- do not inhale or ingest

Stop use and ask a doctor if

- irritation and redness develop
- condition persists for more than 72 hours

Keep out of reach of children.

If swallowed, get medical help or contact a Poison Control Center right away.

Directions

- wet hands thoroughly with product and allow to dry without wiping
- for children under 6, use only under adult supervision
- not recommended for infants

Other information

- do not store above 105⁰F
- may discolor some fabrics
- harmful to wood finishes and plastics

Inactive ingredients

water, glyceryl caprylate/caprate, glycerin, isopropyl myristate, tocopheryl acetate, carbomer or acrylates/C10-30 alkyl acrylate crosspolymer, fragrance, benzophenone-4

Adverse event

*Effective at eliminating more than 99.99% of many common harmful germs and bacteria in as little as 15 seconds.

Distributed by: ULINE

12575 Uline Drive, Pleasant Prairie, WI 53158

1-800-295-5510 - uline.com

Pat. 9,161,982

Principal display panel

ENRICHED WITH MOISTURIZERS

ULINE

Hand Sanitizer

Kills more than 99.99% of germs*

S-21262

2 FL OZ (59 mL)